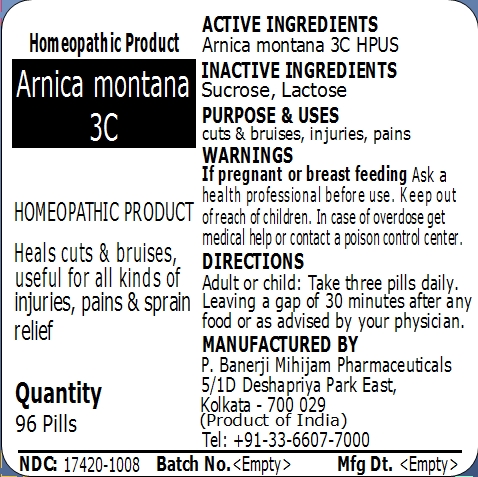 DRUG LABEL: Arnica montana 3C
NDC: 17420-1008 | Form: PELLET
Manufacturer: P. Banerji Mihijam Pharmaceuticals
Category: homeopathic | Type: HUMAN OTC DRUG LABEL
Date: 20141122

ACTIVE INGREDIENTS: ARNICA MONTANA 3 [hp_C]/1 1
INACTIVE INGREDIENTS: SUCROSE; LACTOSE

Principal Display Panel

Homeopathic Product

Arnica montana 3C

Homeopathic Product

Arnica montana 3C

Heals cuts & bruises, useful for all kinds of injuries, pains and sprain relief

Quantity

96 Pills

Active Ingredients

Arnica montana 3C

Inactive Ingredients

Sucrose, Lactose

Purpose

Heals cuts & bruises, useful for all kinds of injuries, pains and sprain relief

Uses

Heals cuts & bruises, useful for all kinds of injuries, pains and sprain relief

Warnings

If pregnant or breast feeding ask a health professional before use.

Keep out of reach of children. In case of overdose get medical help or contact a poison control center.

Direction

Adult or child: Take three pills daily. Leaving a gap of 30 minutes after any food or as advised by your physician.

Manufactured by

P. Banerji Mihijam Pharmaceuticals

5/1D Deshapriya Park East,

Kolkata - 700 029

(Product of INDIA)

+91-33-6607-7000